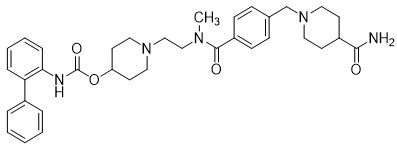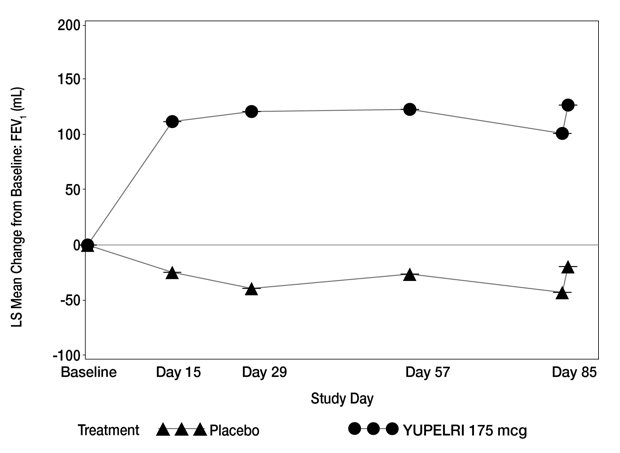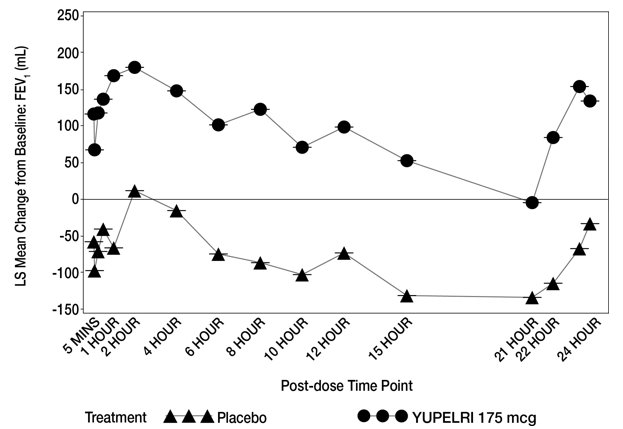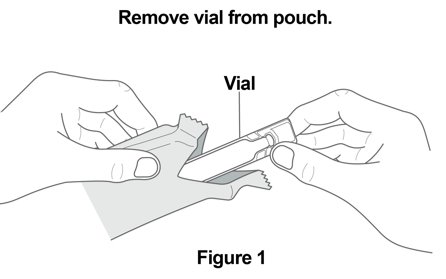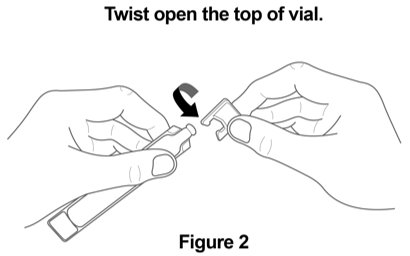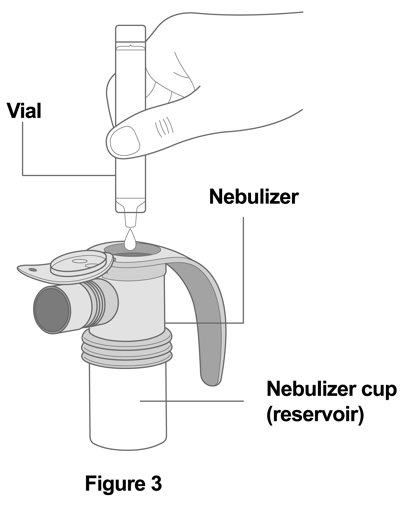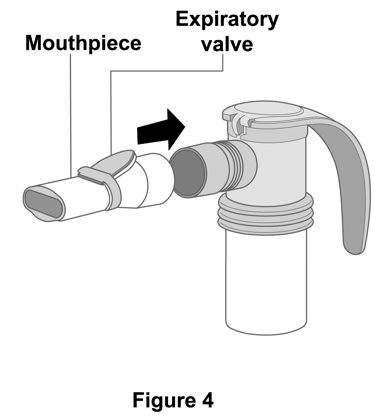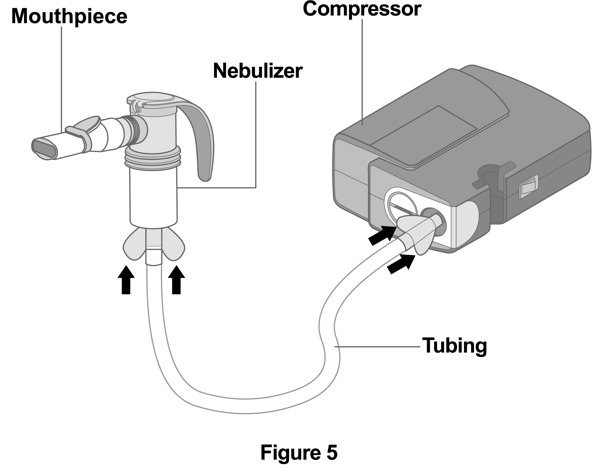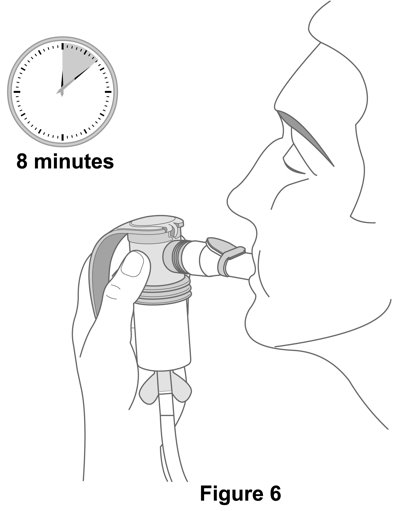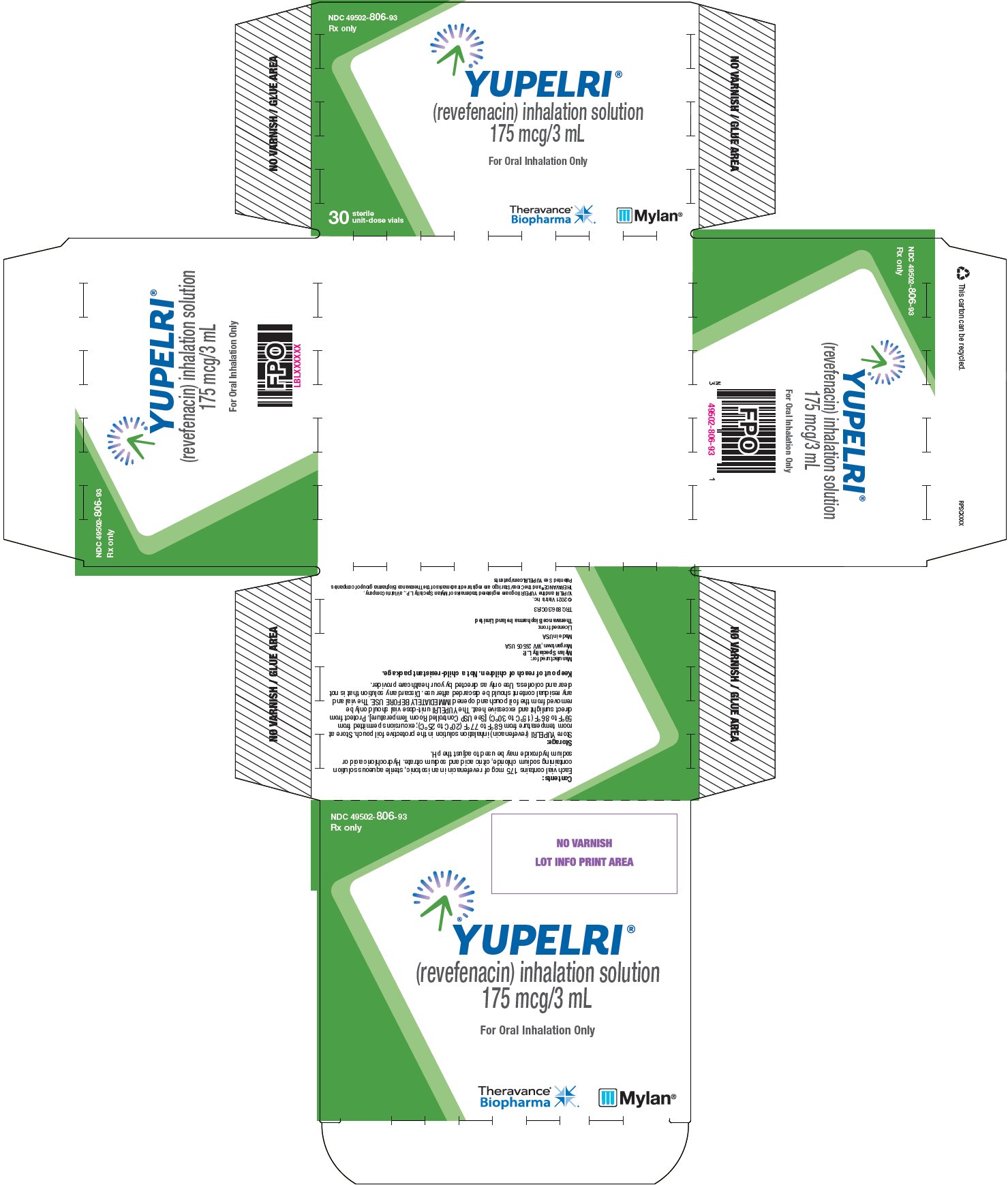 DRUG LABEL: YUPELRI
NDC: 49502-806 | Form: SOLUTION
Manufacturer: Viatris Specialty LLC
Category: prescription | Type: HUMAN PRESCRIPTION DRUG LABEL
Date: 20220503

ACTIVE INGREDIENTS: REVEFENACIN 175 ug/3 mL
INACTIVE INGREDIENTS: SODIUM CHLORIDE; CITRIC ACID MONOHYDRATE; TRISODIUM CITRATE DIHYDRATE; HYDROCHLORIC ACID; SODIUM HYDROXIDE; WATER

HIGHLIGHTS OF PRESCRIBING INFORMATION

These highlights do not include all the information needed to use YUPELRI® safely and effectively. See full prescribing information for YUPELRI.
YUPELRI (revefenacin) inhalation solution, for oral inhalation
Initial U.S. Approval: 2018

1 INDICATIONS AND USAGE

YUPELRI is an anticholinergic indicated for the maintenance treatment of patients with chronic obstructive pulmonary disease (COPD).

2 DOSAGE AND ADMINISTRATION

For oral inhalation use only. Do not swallow YUPELRI.

- One 175 mcg vial (3 mL) once daily. (2)
- For use with a standard jet nebulizer with a mouthpiece connected to an air compressor. (2)

3 DOSAGE FORMS AND STRENGTHS

Inhalation solution: 175 mcg of revefenacin per 3 mL solution in unit dose vials. (3)

4 CONTRAINDICATIONS

YUPELRI is contraindicated in patients with hypersensitivity to revefenacin or any component of this product. (4)

5 WARNINGS AND PRECAUTIONS

- Do not initiate YUPELRI in acutely deteriorating COPD or to treat acute symptoms. (5.1)
- If paradoxical bronchospasm occurs, discontinue YUPELRI and institute alternative therapy. (5.2)
- Worsening of narrow-angle glaucoma may occur. Use with caution in patients with narrow-angle glaucoma and instruct patients to contact a healthcare provider immediately if symptoms occur. (5.3)
- Worsening of urinary retention may occur. Use with caution in patients with prostatic hyperplasia or bladder-neck obstruction and instruct patients to contact a healthcare provider immediately if symptoms occur. (5.4)
- Immediate hypersensitivity reactions may occur. If such a reaction occurs, therapy with YUPELRI should be stopped at once and alternative treatments should be considered. (5.5)

6 ADVERSE REACTIONS

Most common adverse reactions (incidence greater than or equal to 2% and more common than placebo) include cough, nasopharyngitis, upper respiratory tract infection, headache, and back pain. (6.1)

To report SUSPECTED ADVERSE REACTIONS, contact Mylan at 1-877-446-3679 (1-877-4-INFO-RX) or FDA at 1-800-FDA-1088 or www.fda.gov/medwatch.

7 DRUG INTERACTIONS

- Anticholinergics: May interact additively with concomitantly used anticholinergic medications. Avoid administration of YUPELRI with other anticholinergic-containing drugs. (7.1)
- Transporter-related drug interactions: Coadministration of YUPELRI with OATP1B1 and OATP1B3 inhibitors (e.g. rifampicin, cyclosporine, etc.) may lead to an increase in exposure of the active metabolite. Therefore, coadministration with YUPELRI is not recommended. (7.2, 12.3)

8 USE IN SPECIFIC POPULATIONS

Hepatic impairment: Avoid use of YUPELRI in patients with hepatic impairment. (8.6, 12.3)

FULL PRESCRIBING INFORMATION

1 INDICATIONS AND USAGE

YUPELRI is indicated for the maintenance treatment of patients with chronic obstructive pulmonary disease (COPD).

2 DOSAGE AND ADMINISTRATION

The recommended dosage is 175 mcg YUPELRI (one 175 mcg unit‑dose vial) administered by oral inhalation once daily by nebulizer using a mouthpiece.

Administration Overview

YUPELRI should be administered by the orally inhaled route via a standard jet nebulizer connected to an air compressor (See Instructions for Use). The safety and efficacy of YUPELRI have been established in clinical trials when administered using the PARI LC® Sprint nebulizer with a mouthpiece and the PARI Trek® S compressor. The safety and efficacy of YUPELRI delivered from non‑compressor based nebulizer systems have not been established.

The YUPELRI unit-dose vial should only be removed from the foil pouch and opened IMMEDIATELY BEFORE USE. The vial and any residual content should be discarded after use.

No dosage adjustment is required for geriatric patients, or patients with renal impairment [see Use in Specific Populations (8.5, 8.7) and Clinical Pharmacology (12.3)].

The drug compatibility (physical and chemical), efficacy, and safety of YUPELRI when mixed with other drugs in a nebulizer have not been established.

3 DOSAGE FORMS AND STRENGTHS

Inhalation solution: 175 mcg of revefenacin in 3 mL of sterile, clear, colorless, aqueous solution in unit dose vials.

4 CONTRAINDICATIONS

YUPELRI is contraindicated in patients with hypersensitivity to revefenacin or any component of this product.

5 WARNINGS AND PRECAUTIONS

5.1 Deterioration of Disease and Acute Episodes

YUPELRI should not be initiated in patients during acutely deteriorating or potentially life-threatening episodes of COPD. YUPELRI has not been studied in subjects with acutely deteriorating COPD. The initiation of YUPELRI in this setting is not appropriate.

YUPELRI is intended as a once-daily maintenance treatment for COPD and should not be used for relief of acute symptoms, i.e. as rescue therapy for the treatment of acute episodes of bronchospasm, and extra doses should not be used for that purpose. Acute symptoms should be treated with an inhaled, short-acting beta2-agonist.

COPD may deteriorate acutely over a period of hours or chronically over several days or longer. If YUPELRI no longer controls symptoms of bronchoconstriction, the patient's inhaled, short-acting beta2-agonist becomes less effective, or the patient needs more inhalations of a short-acting beta2-agonist than usual, these may be markers of deterioration of disease. In this setting, a re-evaluation of the patient and the COPD treatment regimen should be undertaken at once. Increasing the daily dose of YUPELRI beyond the recommended dose is not appropriate in this situation.

5.2 Paradoxical Bronchospasm

As with other inhaled medicines, YUPELRI can produce paradoxical bronchospasm that may be life-threatening. If paradoxical bronchospasm occurs following dosing with YUPELRI, it should be treated immediately with an inhaled, short-acting bronchodilator; YUPELRI should be discontinued immediately and alternative therapy should be instituted.

5.3 Worsening of Narrow-Angle Glaucoma

YUPELRI should be used with caution in patients with narrow-angle glaucoma. Prescribers and patients should be alert for signs and symptoms of acute narrow-angle glaucoma (e.g. eye pain or discomfort, blurred vision, visual halos or colored images in association with red eyes from conjunctival congestion and corneal edema). Instruct patients to consult a physician immediately if any of these signs or symptoms develops.

5.4 Worsening of Urinary Retention

YUPELRI should be used with caution in patients with urinary retention. Prescribers and patients should be alert for signs and symptoms of urinary retention (e.g. difficulty passing urine, painful urination), especially in patients with prostatic hyperplasia or bladder-neck obstruction. Instruct patients to consult a healthcare provider immediately if any of these signs or symptoms develops.

5.5 Immediate Hypersensitivity Reactions

Immediate hypersensitivity reactions may occur after administration of YUPELRI. If such a reaction occurs, therapy with YUPELRI should be stopped at once and alternative treatments should be considered.

6 ADVERSE REACTIONS

The following clinically significant adverse reactions are described elsewhere in labeling:

- Paradoxical bronchospasm [see Warnings and Precautions (5.2)]
- Worsening of narrow-angle glaucoma [see Warnings and Precautions (5.3)]
- Worsening of urinary retention [see Warnings and Precautions (5.4)]
- Immediate hypersensitivity reactions [see Warnings and Precautions (5.5)]

6.1 Clinical Trial Experience

Because clinical trials are conducted under widely varying conditions, adverse reaction rates observed in the clinical trials of a drug cannot be directly compared to rates in the clinical trials of another drug and may not reflect the rates observed in practice.

The YUPELRI safety database included 2,285 subjects with COPD in two 12-week efficacy studies and one 52-week long-term safety study. A total of 730 subjects received treatment with YUPELRI 175 mcg once daily. The safety data described below are based on the two 12-week trials and the one 52-week trial.

12-Week Trials

YUPELRI was studied in two 12-week replicate placebo-controlled trials in patients with moderate to very severe COPD (Trials 1 and 2). In these trials, 395 patients were treated with YUPELRI at the recommended dose of 175 mcg once daily.

The population had a mean age of 64 years (range from 41 to 88 years), with 50% males, 90% Caucasian, and had COPD with a mean post-bronchodilator forced expiratory volume in one second (FEV1) percent predicted of 55%. Of subjects enrolled in the two 12-week trials, 37% were taking concurrent LABA or ICS/LABA therapy. Patients with unstable cardiac disease, narrow-angle glaucoma, or symptomatic prostatic hypertrophy or bladder outlet obstruction were excluded from these trials.

Table 1 shows the most common adverse reactions that occurred with a frequency of greater than or equal to 2% in the YUPELRI group and higher than placebo in the two 12‑week placebo-controlled trials.

The proportion of subjects who discontinued treatment due to adverse reactions was 13% for the YUPELRI-treated subjects and 19% for placebo-treated subjects.

Table 1: Adverse Reactions with YUPELRI ≥2% Incidence and Higher than Placebo
Adverse Reaction | Placebo; (N = 418) | YUPELRI 175 mcg; (N = 395)
Respiratory, Thoracic and Mediastinal Disorders
Cough | 17 (4%) | 17 (4%)
Infections and Infestations
Nasopharyngitis | 9 (2%) | 15 (4%)
Upper respiratory tract infection | 9 (2%) | 11 (3%)
Nervous System Disorders
Headache | 11 (3%) | 16 (4%)
Musculoskeletal and Connective Tissue Disorders
Back pain | 3 (1%) | 9 (2%)

Other adverse reactions defined as events with an incidence of ≥1.0%, less than 2.0%, and more common than with placebo included the following: hypertension, dizziness, oropharyngeal pain, and bronchitis.

52-Week Trial

YUPELRI was studied in one 52-week, open-label, active-control (tiotropium 18 mcg once daily) trial in 1,055 patients with COPD. In this trial, 335 patients were treated with YUPELRI 175 mcg once daily and 356 patients with tiotropium. The demographic and baseline characteristics of the long-term safety trial were similar to those of the placebo-controlled 12-week studies described, with the exception that concurrent LABA or LABA/ICS therapy was used in 50% of patients. The adverse reactions reported in the long-term safety trial for YUPELRI were consistent with those observed in the placebo-controlled studies of 12-weeks.

6.2 Postmarketing Experience

The following adverse reaction has been reported during post-approval use of YUPELRI. Because this reaction was reported voluntarily from a population of uncertain size, it is not always possible to reliably estimate the frequency or establish a causal relationship to drug exposure.

Gastrointestinal Disorders: Dry mouth

7 DRUG INTERACTIONS

7.1 Anticholinergics

There is potential for an additive interaction with concomitantly used anticholinergic medicines. Therefore, avoid coadministration of YUPELRI with other anticholinergic-containing drugs as this may lead to an increase in anticholinergic adverse effects [see Warnings and Precautions (5.3, 5.4)].

7.2 Transporter-Related Drug Interactions

OATP1B1 and OATP1B3 inhibitors (e.g. rifampicin, cyclosporine, etc.) could lead to an increase in systemic exposure of the active metabolite. Therefore, coadministration with YUPELRI is not recommended [see Clinical Pharmacology (12.3)].

8 USE IN SPECIFIC POPULATIONS

8.1 Pregnancy

Risk Summary

There are no adequate and well-controlled studies with YUPELRI in pregnant women. Women should be advised to contact their physician if they become pregnant while taking YUPELRI. In animal reproduction studies, subcutaneous administration of revefenacin to pregnant rats and rabbits during the period of organogenesis produced no evidence of fetal harm at respective exposures approximately 209 times the exposure at the maximum recommended human dose (MRHD) (on an area under the curve [AUC] basis) (see Data).

The estimated background risk of major birth defects and miscarriage for the indicated population is unknown. In the U.S. general population, the estimated background risk of major birth defects and miscarriage in clinically recognized pregnancies is 2-4% and 15-20%, respectively.

Data

Animal Data

In an embryo‑fetal development study in pregnant rats dosed during the period of organogenesis from gestation days 6 to 17, revefenacin was not teratogenic and did not affect fetal survival at exposures up to 209 times the MRHD (based upon summed AUCs for revefenacin and its active metabolite at maternal subcutaneous doses up to 500 mcg/kg/day).

In an embryo‑fetal development study in pregnant rabbits dosed during the period of organogenesis from gestation days 7 to 19, revefenacin was not teratogenic and did not affect fetal survival at exposures up to 694 times the MRHD (based upon summed AUCs for revefenacin and its active metabolite at maternal subcutaneous doses up to 500 mcg/kg/day).

Placental transfer of revefenacin and its active metabolite was observed in pregnant rabbits.

In a pre- and postnatal development (PPND) study in pregnant rats dosed during the periods of organogenesis and lactation from gestation day 6 to lactation day 20, revefenacin had no adverse developmental effects on pups at exposures up to 196 times the MRHD (based upon summed AUCs for revefenacin and its active metabolite at maternal subcutaneous doses up to 500 mcg/kg/day).

8.2 Lactation

Risk Summary

There is no information regarding the presence of revefenacin in human milk, the effects on the breastfed infant, or the effects on milk production. However, revefenacin was present in the milk of lactating rats following dosing during pregnancy and lactation (see Data).

The developmental and health benefits of breastfeeding should be considered along with the mother’s clinical need for YUPELRI and any potential adverse effects on the breastfed infant from YUPELRI or from the underlying maternal condition.

Data

Animal Data

In a PPND study [see Pregnancy (8.1)], revefenacin and its active metabolite were present in milk of lactating rats on lactation day 22. Milk-to-plasma concentration ratios were up to 10 for revefenacin and its active metabolite.

8.4 Pediatric Use

The safety and effectiveness of YUPELRI have not been established in pediatric patients. YUPELRI is not indicated for use in children.

8.5 Geriatric Use

Based on available data, no adjustment of the dosage of YUPELRI in geriatric patients is necessary.

Clinical trials of YUPELRI included 441 subjects aged 65 years and older, and of those, 101 subjects were aged 75 years and older. No overall differences in safety or effectiveness were observed between these subjects and younger subjects, and other reported clinical experience has not identified differences in responses between the elderly and younger patients, but greater sensitivity of some older individuals cannot be ruled out.

8.6 Hepatic Impairment

The systemic exposure of revefenacin is unchanged while that of its active metabolite is increased in subjects with moderate hepatic impairment. The safety of YUPELRI has not been evaluated in COPD patients with mild-to-severe hepatic impairment. YUPELRI is not recommended in patients with any degree of hepatic impairment. [see Clinical Pharmacology (12.3)].

8.7 Renal Impairment

No dosage adjustment is required in patients with renal impairment. Monitor for systemic antimuscarinic side effects in COPD patients with severe renal impairment. [see Clinical Pharmacology (12.3)].

10 OVERDOSAGE

An overdosage of YUPELRI may lead to anticholinergic signs and symptoms such as nausea, vomiting, dizziness, lightheadedness, blurred vision, increased intraocular pressure (causing pain, vision disturbances, or reddening of the eye), obstipation or difficulties in voiding.

Treatment of overdosage consists of discontinuation of YUPELRI along with institution of appropriate symptomatic and/or supportive therapy.

11 DESCRIPTION

YUPELRI is a sterile, clear, colorless, aqueous solution of revefenacin. Revefenacin, the active component of YUPELRI, is an anticholinergic. The chemical name for revefenacin is 1-(2-{4-[(4-carbamoylpiperidin-1-yl)methyl]-N-methylbenzamido}ethyl)piperidin-4-yl N-({1,1’-biphenyl}-2-yl)carbamate; its structural formula is:

Revefenacin has a molecular weight of 597.76 and its empirical formula is C35H43N5O4. Revefenacin is a white to off-white crystalline powder and is slightly soluble in water.

YUPELRI is supplied as 3 mL of revefenacin solution packaged in a unit-dose low-density polyethylene vial overwrapped in a foil pouch. Each vial contains 175 mcg of revefenacin in 3 mL of an isotonic, sterile aqueous solution containing citric acid, sodium chloride, sodium citrate, and water for injection at pH 5.0. Hydrochloric acid or sodium hydroxide may be used to adjust the pH.

YUPELRI does not require dilution prior to administration by nebulization. Like all other nebulized treatments, the amount delivered to the lungs will depend on patient factors, the nebulization system used, and compressor performance.

Using the PARI LC® Sprint nebulizer connected to a PARI Trek® S compressor under in vitro conditions, the mean delivered dose from the mouthpiece was approximately 62 mcg (35% of label claim), at a mean flow rate of 4 LPM. The mean nebulization time was 8 minutes. YUPELRI should only be administered via a standard jet nebulizer connected to an air compressor with an adequate airflow, and equipped with a mouthpiece.

12 CLINICAL PHARMACOLOGY

12.1 Mechanism of Action

Revefenacin is a long-acting muscarinic antagonist, which is often referred to as an anticholinergic. It has similar affinity to the subtypes of muscarinic receptors M1 to M5. In the airways, it exhibits pharmacological effects through inhibition of M3 receptor at the smooth muscle leading to bronchodilation. The competitive and reversible nature of antagonism was shown with human and animal origin receptors and isolated organ preparations. In preclinical in vitro as well as in vivo models, prevention of methacholine- and acetylcholine-induced bronchoconstrictive effects was dose-dependent and lasted longer than 24 hours. The clinical relevance of these findings is unknown. The bronchodilation following inhalation of revefenacin is predominantly a site-specific effect.

12.2 Pharmacodynamics

Cardiac Electrophysiology

QTc interval prolongation was studied in a randomized, double-blind, placebo- and positive‑controlled, single dose, crossover trial in 48 healthy subjects. Following a single dose of revefenacin 700 mcg (4 times the recommended dosage), no effects on prolongation of QTc interval were observed.

12.3 Pharmacokinetics

Revefenacin pharmacokinetic parameters are presented as the mean [standard deviation (SD)] unless otherwise specified. Following repeat dosing of inhaled YUPELRI, steady-state was achieved within 7 days with <1.6‑fold accumulation. Revefenacin exposure (Cmax and AUC) in COPD patients is approximately 60% lower as compared to healthy subjects. Exposure (Cmax and AUC) of the active metabolite in COPD patients is approximately 2-fold higher as compared to healthy subjects. Revefenacin Cmax was 0.16 ng/mL (0.11) and AUC was 0.22 ng·hr/mL (0.20) at steady-state after inhaled YUPELRI 175 mcg dose in COPD patients. Cmax of the active metabolite was 0.20 ng/mL (0.13) and AUC was 0.69 ng·hr/mL (0.53) at steady-state after inhaled YUPELRI 175 mcg dose in COPD patients.

Revefenacin and its active metabolite exposure increased in a slightly greater than dose proportional manner with increasing revefenacin dose. After single or multiple once-daily dosing of YUPELRI, both AUC and Cmax of revefenacin and its active metabolite increased by approximately 11-fold over the 88 to 700 mcg (8‑fold) dose range.

Absorption

Following inhaled administration of YUPELRI in healthy subjects or COPD patients, Cmax of revefenacin and its active metabolite occurred at the first postdose sampling time which ranged from 14 to 41 minutes after start of nebulization. The absolute bioavailability following an oral dose of revefenacin is low (<3%).

Distribution

Following intravenous administration to healthy subjects, the mean steady-state volume of distribution of revefenacin was 218 L suggesting extensive distribution to tissues. In vitro protein binding of revefenacin and its active metabolite in human plasma was on average 71% and 42%, respectively.

Elimination

The terminal half-life of revefenacin and its active metabolite after once-daily dosing of YUPELRI in COPD patients is 22 to 70 hours.

Metabolism

In vitro and in vivo data showed that revefenacin is primarily metabolized via hydrolysis of the primary amide to a carboxylic acid forming its major active metabolite. Following inhaled administration of YUPELRI in COPD patients, conversion to its active metabolite occurred rapidly, and plasma exposures of the active metabolite exceeded those of revefenacin by approximately 4- to 6-fold (based on AUC). The active metabolite is formed by hepatic metabolism and possesses activity at target muscarinic receptors that is lower (approximately one-third to one-tenth) than that of revefenacin. It could potentially contribute to systemic antimuscarinic effects at therapeutic doses.

Excretion

Following administration of a single intravenous dose of radiolabeled revefenacin to healthy male subjects, approximately 54% of total radioactivity was recovered in the feces and 27% was excreted in the urine. Approximately 19% of the administered radioactive dose was recovered in the feces as the active metabolite. Following administration of a single radiolabeled oral dose of revefenacin, 88% of total radioactivity was recovered in the feces and <5% was present in urine, suggesting low oral absorption. There was minimal renal excretion (<1%) of revefenacin and its active metabolite following inhaled administration of YUPELRI in COPD patients.

Specific Populations

Population pharmacokinetic analysis showed no evidence of a clinically significant effect of age (44 to 79 years), gender (59% male), smoking status (42% current smoker), or weight (46 to 155 kg) on systemic exposure of revefenacin and its active metabolite.

Patients with Hepatic Impairment

The pharmacokinetics of YUPELRI was evaluated in subjects with moderate hepatic impairment (Child-Pugh score of 7-9). There was no increase in Cmax of revefenacin and 1.5-fold increase in Cmax of the active metabolite. There was 1.2-fold increase in AUC of revefenacin and up to 4.7-fold increase in AUC of the active metabolite. YUPELRI has not been evaluated in subjects with severe hepatic impairment.

Patients with Renal Impairment

The pharmacokinetics of YUPELRI was evaluated in subjects with severe renal impairment (CrCl <30 mL/min). There was 1.5-fold increase in Cmax of revefenacin and up to 2-fold increase in Cmax of the active metabolite. There was up to 2.3‑fold increase in AUCinf of revefenacin; the active metabolite exposure (AUCinf) was increased by up to 2.5-fold. YUPELRI has not been evaluated in subjects with end-stage renal disease.

Drug Interaction Studies

Revefenacin and Cytochrome P450

Neither revefenacin nor its active metabolite inhibits the following cytochrome P450 isoforms: CYP1A2, CYP2B6, CYP2C8, CYP2C9, CYP2C19, CYP2D6, and CYP3A4/5. Neither revefenacin nor its active metabolite induces CYP1A2, CYP2B6, and CYP3A4/5.

Revefenacin and Efflux Transporters

Revefenacin is a substrate of P-gp and BCRP. Neither revefenacin nor its active metabolite is an inhibitor of these efflux transporters.

Revefenacin and Uptake Transporters

The active metabolite of revefenacin is a substrate of OATP1B1 and OATP1B3. Neither revefenacin nor its active metabolite is an inhibitor of the uptake transporters OATP1B1, OATP1B3, OAT1, OAT3, or OCT2.

13 NONCLINICAL TOXICOLOGY

13.1 Carcinogenesis, Mutagenesis, Impairment of Fertility

Two-year inhalation studies in Sprague-Dawley rats and CD1 mice were conducted to assess the carcinogenic potential of revefenacin. No evidence of tumorigenicity was observed in male and female rats at inhaled doses up to 338 mcg/kg/day (approximately 35 times the MRHD based upon summed AUCs for revefenacin and its active metabolite). No evidence of tumorigenicity was observed in male and female mice at inhaled doses up to 326 mcg/kg/day (approximately 40 times the MRHD based on summed AUCs for revefenacin and its active metabolite).

Revefenacin and its active metabolite were negative for mutagenicity in the Ames test for bacterial gene mutation. Revefenacin was negative for genotoxicity in the in vitro mouse lymphoma assay and in vivo rat bone marrow micronucleus assay.

There were no effects on male or female fertility and reproductive performance in rats at subcutaneous revefenacin doses up to 500 mcg/kg/day (approximately 30 times the MRHD on an mg/m^2 basis for revefenacin).

14 CLINICAL STUDIES

The safety and efficacy of YUPELRI 175 mcg once daily were evaluated in two dose‑ranging trials, two replicate 12-week, Phase 3 confirmatory clinical trials, and a 52-week safety trial. The efficacy of YUPELRI is primarily based on the two replicate 12-week, Phase 3 placebo-controlled trials in 1,229 subjects with COPD.

14.1 Dose-Ranging Trials

Dose selection for YUPELRI was supported by a 28-day, randomized, double-blind, placebo-controlled, parallel-group trial of 355 subjects diagnosed with moderate to severe COPD, which was conducted to evaluate four doses of YUPELRI. YUPELRI 44, 88, 175, and 350 mcg, or matching placebo were taken once daily in the morning via a standard jet nebulizer (PARI LC® Sprint Reusable Nebulizer) and evaluated using the primary efficacy endpoint of change from baseline in trough (predose) FEV1 measured on Day 29. The LS mean differences in change from baseline in trough FEV1 compared to placebo for the 44 mcg, 88 mcg, 175 mcg, and 350 mcg once-daily doses were 52 mL [95% CI: -17.3, 121.0], 187 mL [95% CI: 118.8, 256.1], 167 mL [95% CI: 97.3, 236.0], and 171 mL [95% CI: 101.9, 239.3], respectively.

Evaluations of the dosing interval by comparing once- and twice-daily dosing of YUPELRI in a 7-day, randomized, double-blind, placebo-controlled, crossover trial in 64 patients supported selection of the once-daily dosing interval for further evaluation in the confirmatory COPD trials.

The dose-ranging results supported the evaluation of two doses of YUPELRI, 88 mcg and 175 mcg once daily, in the confirmatory COPD trials.

14.2 Confirmatory Trials

The clinical development program for YUPELRI included two 12-week, randomized, double-blind, placebo-controlled, multiple-dose, parallel-group, confirmatory trials in subjects with moderate to very severe COPD designed to evaluate the efficacy of once-daily YUPELRI’s effect on lung function (Trial 1: NCT02459080 and Trial 2: NCT02512510). To be enrolled, subjects needed to be 40 years of age or older, have a clinical diagnosis of COPD, a history of smoking greater than or equal to 10 pack-years, moderate to very severe COPD (post‑ipratropium FEV1 less than or equal to 80% of predicted normal values but at least 700 mL), and an FEV1/FVC ratio of 0.7 or less. Trials 1 and 2 included 1,229 subjects of which 395 received the 175 mcg dose administered via a standard jet nebulizer (PARI LC® Sprint Reusable Nebulizer). The study population had a mean age of 64 years (range: 41 to 88) and mean smoking history of 53 pack-years, with 48% identified as current smokers. At screening, the mean post-bronchodilator percent predicted FEV1 was 55% (range: 10% to 90%), and the post-bronchodilator FEV1/FVC ratio was 0.54 (range: 0.3 to 0.7). In addition, of the subjects enrolled, 37% were taking LABA or ICS/LABA therapy at study entry and remained on this concomitant therapy throughout the study.

Trials 1 and 2 evaluated YUPELRI 175 mcg once daily and placebo once daily. The primary endpoint was change from baseline in trough (predose) FEV1 at Day 85. In both trials, YUPELRI 175 mcg demonstrated significant improvement in lung function (mean change from baseline in trough (predose) FEV1) compared to placebo.

Table 2 presents the results from Trial 1 and Trial 2. The change from baseline in trough FEV1 over time from Trial 1 is depicted in Figure 1.

Table 2: LS Mean Change from Baseline in Trough FEV1 (mL) on Day 85 (ITT)
 | Trial 1 |  | Trial 2
 | Placebo; (N = 209) | YUPELRI 175 mcg QD (N = 198) | Placebo; (N = 208) | YUPELRI 175 mcg QD (N = 197)
n [n=subjects in ITT population used in the statistical analyses.] | 191 | 189 | 187 | 181
LS Mean (SE) | -19 (16.1) | 127 (15.4) | -45 (18.8) | 102 (18.5)
LS Mean Difference (SE) from Placebo | -- | 146 (21.6) | -- | 147 (25.5)
95% CI for LS Mean Difference from Placebo | -- | (103.7, 188.8) | -- | (97.0, 197.1)
LS – Least Square, SE – Standard Error

Figure 1: LS Mean Change from Baseline in Trough FEV1 (mL) over 12 Weeks (Trial 1)

In Trial 1, serial spirometry over 24 hours was performed in a subset of patients (n=44 placebo, n=45 YUPELRI 175 mcg) on Day 84. In Trial 2, similar testing was also performed (n=39 placebo, n=44 YUPELRI 175 mcg). That data for Trial 1 is shown in Figure 2.

Figure 2: LS Mean Change from Baseline FEV1 (mL) over 24 Hours Day 84 (Trial 1 subset)

Peak FEV1 was defined as the highest postdose FEV1 within the first 2 hours after dosing on Day 1. The mean peak FEV1 improvement on Day 1 relative to placebo was 133 mL and 129 mL in Trials 1 and 2, respectively.

The St. Georges Respiratory Questionnaire (SGRQ) was assessed in Trials 1 and 2. In Trial 1, the SGRQ responder rate (defined as an improvement in score of 4 or more as threshold) for the YUPELRI treatment arm on Day 85 was 49% compared to 34% for placebo [Odds Ratio: 2.11; 95% CI: 1.14, 3.92]. In Trial 2, the SGRQ responder rate for the YUPELRI treatment arm was 45% compared to 39% for placebo [Odds Ratio: 1.31; 95% CI: 0.72, 2.38].

16 HOW SUPPLIED/STORAGE AND HANDLING

Inhalation solution: YUPELRI is supplied as a 175 mcg/3 mL sterile, clear, colorless, aqueous solution in unit-dose low‑density polyethylene vials. Each vial is overwrapped in a foil pouch and supplied in cartons containing either 30 individually pouched unit‑dose vials (NDC 49502-806-93) or 7 individually pouched unit-dose vials (NDC 49502-806-77).

Storage and Handling

- Store YUPELRI in the protective foil pouch.
- Store at room temperature from 68°F to 77°F (20°C to 25°C); excursions permitted from 59°F to 86°F (15°C to 30°C) [See USP Controlled Room Temperature]. Protect from direct sunlight and excessive heat.

The YUPELRI solution unit-dose vial should only be removed from the foil pouch and opened IMMEDIATELY BEFORE USE. The vial and any residual content should be discarded after use.

- Discard any solution that is not clear and colorless.
- YUPELRI should only be administered via a standard jet nebulizer connected to an air compressor with an adequate airflow, and equipped with a mouthpiece.
- Do not swallow or inject YUPELRI.

17 PATIENT COUNSELING INFORMATION

Advise the patient to read the FDA-approved patient labeling (Patient Information and Instructions for Use).

Not for Acute Symptoms

Inform patients that YUPELRI is not meant to relieve acute symptoms of COPD and extra doses should not be used for that purpose. Advise patients to treat acute symptoms with an inhaled, short-acting beta2-agonist such as albuterol [see Warnings and Precautions (5.1)]. Provide patients with such medicine and instruct them in how it should be used.

Instruct patients to seek medical attention immediately if they experience any of the following:

- Decreasing effectiveness of inhaled, short-acting beta2-agonists
- Need for more inhalations than usual of inhaled, short-acting beta2-agonists
- Significant decrease in lung function as outlined by the physician

Tell patients they should not stop therapy with YUPELRI without healthcare provider guidance since symptoms may recur after discontinuation.

Paradoxical Bronchospasm

As with other inhaled medicines, YUPELRI can cause paradoxical bronchospasm. If paradoxical bronchospasm occurs, instruct patients to discontinue YUPELRI [see Warnings and Precautions (5.2)].

Worsening of Narrow-Angle Glaucoma

Instruct patients to be alert for signs and symptoms of acute narrow-angle glaucoma (e.g. eye pain or discomfort, blurred vision, visual halos, or colored images in association with red eyes from conjunctival congestion and corneal edema). Instruct patients to consult a healthcare provider immediately if any of these signs or symptoms develops [see Warnings and Precautions (5.3)].

Worsening of Urinary Retention

Instruct patients to be alert for signs and symptoms of urinary retention (e.g. difficulty passing urine, painful urination). Instruct patients to consult a healthcare provider immediately if any of these signs or symptoms develops [see Warnings and Precautions (5.4)].

Instructions for Administering YUPELRI

It is important for patients to understand how to correctly administer YUPELRI using a standard jet nebulizer [see Instructions for Use]. Instruct patients that YUPELRI should only be administered via a standard jet nebulizer. Patients should be instructed not to inject or swallow the YUPELRI solution. Patients should be instructed not to mix other medications with YUPELRI.

Patients should not inhale more than one dose at any one time. The daily dosage of YUPELRI should not exceed one unit-dose vial. Inform patients to use the contents of one vial of YUPELRI orally inhaled daily at the same time every day. Patients should throw the plastic dispensing vials away immediately after use. Due to their small size, the vials pose a danger of choking to young children.

The brands listed are trademarks of their respective owners.

Licensed from:
Theravance Biopharma Ireland Limited

Manufactured for:
Mylan Specialty L.P.
Morgantown, WV 26505 USA

Made in USA
© 2021 Viatris Inc.

YUPELRI® is a registered trademark of Mylan Specialty L.P., a Viatris Company.

Patented. See YUPELRI.com/ patents

PATIENT INFORMATION

YUPELRI® (you-PELL-ree)

(revefenacin) inhalation solution, for oral inhalation

Important: For oral inhalation only. Do not swallow or inject YUPELRI.

What is YUPELRI?

- YUPELRI is a prescription medicine used to treat chronic obstructive pulmonary disease (COPD). COPD is a long-term (chronic) lung disease that includes chronic bronchitis, emphysema, or both.
- YUPELRI is an anticholinergic medicine. Anticholinergic medicines help the muscles around the airways in your lungs stay relaxed to prevent symptoms such as wheezing, cough, chest tightness, and shortness of breath.
- YUPELRI is used long-term as 1 vial of YUPELRI, 1 time each day inhaled through your nebulizer to improve symptoms of COPD for better breathing.
- YUPELRI is not used to relieve sudden breathing problems and will not replace an inhaled rescue medicine.
- YUPELRI should not be used in children. It is not known if YUPELRI is safe and effective in children.

Do not use YUPELRI if you have had an allergic reaction to revefenacin or any of the ingredients in YUPELRI. Ask your healthcare provider if you are not sure. See the end of this Patient Information leaflet for a complete list of ingredients in YUPELRI.

Before using YUPELRI, tell your healthcare provider about all your medical conditions, including if you:

- have eye problems such as glaucoma. YUPELRI may make your glaucoma worse.
- have prostate or bladder problems, or problems passing urine. YUPELRI may make these problems worse.
- have liver problems.
- are allergic to any of the ingredients in YUPELRI or any other medicines. See “What are the ingredients in YUPELRI?” below for a complete list of ingredients.
- are pregnant or plan to become pregnant. It is not known if YUPELRI may harm your unborn baby.
- are breastfeeding. It is not known if the medicine in YUPELRI passes into your breast milk and if it can harm your baby.

Tell your healthcare provider about all the medicines you take, including prescription and over-the-counter medicines, vitamins, and herbal supplements. YUPELRI and certain other medicines may interact with each other. This may cause serious side effects.

Especially tell your healthcare provider if you take:

- other anticholinergic medicines (including tiotropium, ipratropium, aclidinium, umeclidinium, glycopyrrolate)
- atropine

Know the medicines you take. Keep a list of them to show your healthcare provider and pharmacist each time you get a new medicine.

How should I use YUPELRI?

Read the step-by-step instructions for using YUPELRI at the end of this Patient Information leaflet.

- YUPELRI is only for use with a nebulizer.
- Do not use YUPELRI unless your healthcare provider has taught you how to use it with your nebulizer and you understand how to use it correctly.
- Use YUPELRI exactly as your healthcare provider tells you to use it. Do not use YUPELRI more often than prescribed.
- YUPELRI is taken as a breathing treatment (by oral inhalation) and should be used with a standard jet nebulizer with a mouthpiece connected to an air compressor.
- Do not mix YUPELRI with other medicines in your nebulizer.
- Use 1 vial of YUPELRI, 1 time each day. Do not use more than 1 vial of YUPELRI a day.
- Use YUPELRI at the same time each day.
- If you use too much YUPELRI, call your healthcare provider or go to the nearest hospital emergency room right away if you have any unusual symptoms, such as worsening shortness of breath, chest pain, or increased heart rate.
- Do not use other medicines that contain an anticholinergic for any reason. Ask your healthcare provider or pharmacist if any of your other medicines are anticholinergic medicines.
- YUPELRI does not relieve sudden symptoms of COPD and you should not use extra doses of YUPELRI to relieve these sudden symptoms. Always have an inhaled rescue medicine with you to treat sudden symptoms. If you do not have an inhaled rescue medicine, call your healthcare provider to have one prescribed for you.
- Do not stop using YUPELRI, even if you are feeling better, unless your healthcare provider tells you to because your symptoms might get worse.
- Call your healthcare provider or get emergency medical care right away if:
  - your breathing problems get worse.
  - you need to use your inhaled rescue medicine more often than usual.
  - your inhaled rescue medicine does not relieve your symptoms.

What are the possible side effects with YUPELRI?

YUPELRI can cause serious side effects, including:

- Sudden breathing problems immediately after inhaling your medicine. If you have sudden breathing problems immediately after inhaling your medicine, stop using YUPELRI and call your healthcare provider right away.
- New or worsened eye problems including acute narrow-angle glaucoma. Acute narrow-angle glaucoma can cause permanent loss of vision if not treated. Symptoms of acute narrow-angle glaucoma may include:

- red eyes
- blurred vision
- seeing halos or bright colors around lights

- eye pain or discomfort
- nausea or vomiting

If you have any of these symptoms, call your healthcare provider right away before using another dose of YUPELRI.
1. Urinary retention. People who use YUPELRI may develop new or worse urinary retention. Symptoms of urinary retention may include:

- difficulty urinating
- urinating frequently

- urination in a weak stream or drips
- painful urination

If you have any of these symptoms, call your healthcare provider right away before using another dose of YUPELRI.
1. Serious allergic reactions. See “Do not use YUPELRI if you have had an allergic reaction to revefenacin or any of the ingredients in YUPELRI.”
Call your healthcare provider or get emergency medical care if you get any of the following symptoms of a serious allergic reaction:

- rash
- hives
- severe itching

- swelling of your face, mouth, and tongue
- difficulty breathing or swallowing

- Common side effects of YUPELRI include:

- cough
- runny nose
- upper respiratory tract infection

- headache
- back pain

These are not all the possible side effects of YUPELRI.

Call your doctor for medical advice about side effects. You may report side effects to FDA at 1‑800-FDA-1088.

How should I store YUPELRI?

- Store YUPELRI at room temperature between 68°F to 77°F (20°C to 25°C).
- Store YUPELRI in the unopened protective foil pouch and only open the foil pouch right before you are ready to use YUPELRI.
- Keep YUPELRI away from light and heat.
- Throw away the vial of YUPELRI and any leftover medicine after use.
- Throw away the vial of YUPELRI if the solution is not clear and colorless.
- Do not use YUPELRI after the expiration date provided on the foil pouch and vial.
- Keep YUPELRI and all medicines out of the reach of children.

General Information about the safe and effective use of YUPELRI.

Medicines are sometimes prescribed for purposes other than those listed in a Patient Information leaflet. Do not use YUPELRI for a condition for which it was not prescribed. Do not give YUPELRI to other people, even if they have the same symptoms that you have. It may harm them.

You can ask your healthcare provider or pharmacist for information about YUPELRI that is written for health professionals.

What are the ingredients in YUPELRI?

Active ingredient: revefenacin

Inactive ingredients: sodium chloride, citric acid, sodium citrate, and water for injection. Hydrochloric acid or sodium hydroxide may be used to adjust the pH.

Licensed from:
Theravance Biopharma Ireland Limited

Manufactured for:
Mylan Specialty L.P.
Morgantown, WV 26505 USA

Made in USA

© 2021 Viatris Inc.

YUPELRI® is a registered trademark of Mylan Specialty L.P., a Viatris Company.

Patented. See YUPELRI.com/patents

For more information about YUPELRI, go to www.YUPELRI.com or call 1-877-446-3679 (1-877-4-INFO-RX).

This Patient Information has been approved by the U.S. Food and Drug Administration. Revised: 11/2021

INSTRUCTIONS FOR USE
YUPELRI® (you-PELL-ree)
(revefenacin)
inhalation solution, for oral inhalation

YUPELRI is used only in a standard jet nebulizer machine with a mouthpiece connected to an air compressor. Make sure you know how to use your nebulizer machine before you use it to breathe in YUPELRI or other medicines.

Important Information:

- Do not mix YUPELRI with other medicines in your nebulizer.
- YUPELRI comes in a vial that is sealed in a foil pouch. Do not open the sealed pouch until you are ready to use a dose of YUPELRI.
- Use your YUPELRI right away after opening.

Using YUPELRI:

Read the following Steps before using YUPELRI. If you have any questions, ask your healthcare provider or pharmacist.

Step 1.Open Pouch: Open the foil pouch by tearing along the seam of the pouch. Remove the vial of YUPELRI from the foil pouch (Figure 1).

Step 2. Open Vial: Carefully twist open the top of the vial and use it right away (Figure 2).

Step 3. Add Medicine: Squeeze all of the medicine from the vial into the nebulizer cup (reservoir) (Figure 3).

Step 4. Attach Mouthpiece: Connect the mouthpiece to the nebulizer cup (reservoir) with the expiratory valve facing up (Figure 4).

Step 5. Connect the Nebulizer to the Compressor: Firmly insert one end of the tubing to the compressor. Insert the other end of the tubing to the bottom of the nebulizer cup (reservoir) (Figure 5).

Step 6. Prepare for Treatment: Sit in a comfortable, upright position. Place the mouthpiece in your mouth and close your lips around the mouthpiece.

Step 7. Begin Treatment: Turn on the compressor to begin your treatment (Figure 6).

Step 8. Breathe in Medicine: Breathe as calmly, deeply, and evenly as possible until no more mist is seen in the nebulizer reservoir. Your treatment will take about 8 minutes. When you do not see any mist in the nebulizer, your treatment is finished. Turn the compressor off.

Step 9. Clean Nebulizer: Clean and store your nebulizer. See the manufacturer’s instructions that come with your nebulizer for how to clean and store your nebulizer.

This Instructions for Use has been approved by the U.S. Food and Drug Administration.

Licensed from:
Theravance Biopharma Ireland Limited

Manufactured for:
Mylan Specialty L.P.
Morgantown, WV 26505 USA

Made in USA

© 2021 Viatris Inc.

YUPELRI® is a registered trademark of Mylan Specialty L.P., a Viatris Company.

Patented. See YUPELRI.com/patents

Revised: 5/2022
MS:RVFN:R4

RPINXXXX

PRINCIPAL DISPLAY PANEL – 175mcg/3 mL

NDC 49502-806-93
Rx only

YUPELRI®
(revefenacin) inhalation solution
175 mcg/3 mL

For Oral Inhalation Only

30 sterile
unit-dose vials

Contents:
Each vial contains 175 mcg of revefenacin in an isotonic, sterile aqueous solution containing sodium chloride, citric acid and sodium citrate. Hydrochloric acid or sodium hydroxide may be used to adjust the pH.

Storage:
Store YUPELRI (revefenacin) inhalation solution in the protective foil pouch. Store at room temperature from 68°F to 77°F (20°C to 25°C); excursions permitted from 59°F to 86°F (15°C to 30°C) [See USP Controlled Room Temperature]. Protect from direct sunlight and excessive heat. The YUPELRI unit-dose vial should only be removed from the foil pouch and opened IMMEDIATELY BEFORE USE. The vial and any residual content should be discarded after use. Discard any solution that is not clear and colorless. Use only as directed by your healthcare provider.

Keep out of reach of children. Not a child-resistant package.

Manufactured for:
Mylan Specialty L.P.
Morgantown, WV 26505 USA
Made in USA

Licensed from:
Theravance Biopharma Ireland Limited

TRC:806:30C:R3

© 2021 Viatris Inc.

YUPELRI and the YUPELRI logo are registered trademarks of Mylan Specialty L.P., a Viatris Company.

THERAVANCE® and the Cross/Star logo are registered trademarks of the Theravance Biopharma group of companies.

Patented. See YUPELRI.com/patents